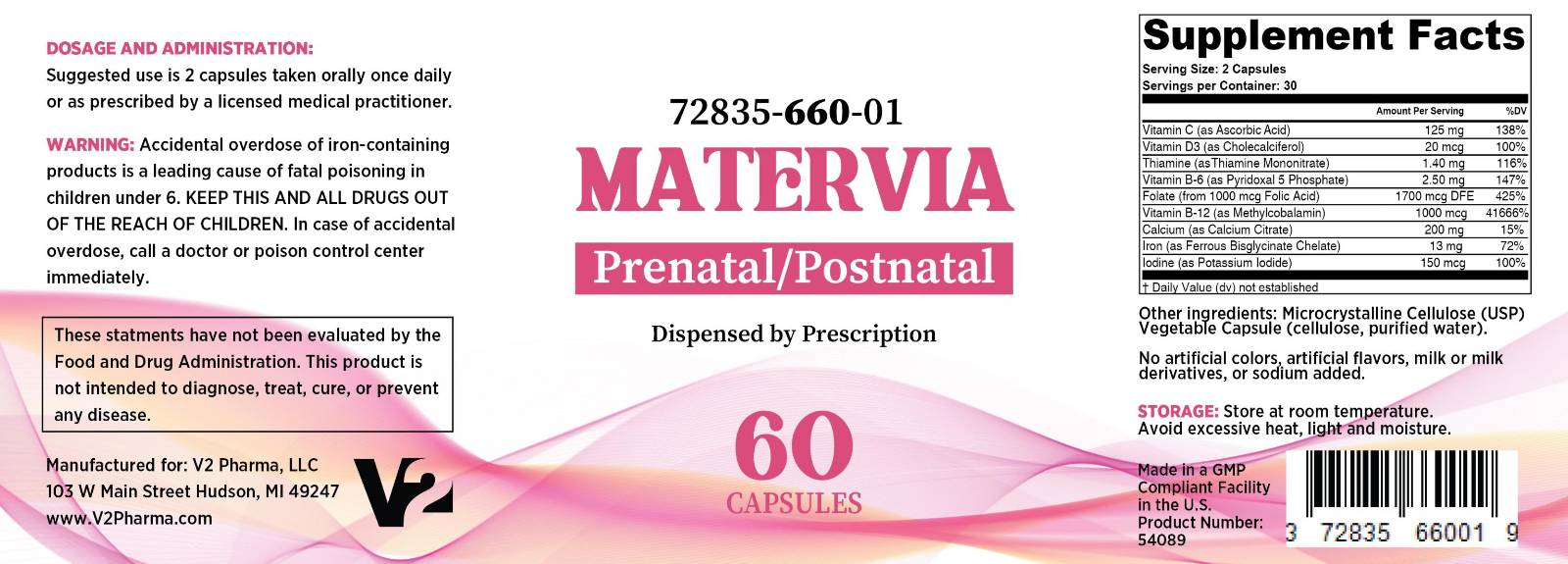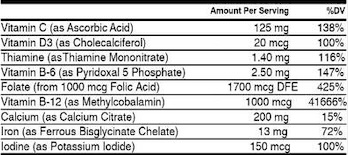 DRUG LABEL: Matervia
NDC: 72835-660 | Form: CAPSULE
Manufacturer: V2 Pharma LLC
Category: prescription | Type: HUMAN PRESCRIPTION DRUG LABEL
Date: 20250611

ACTIVE INGREDIENTS: ASCORBIC ACID 125 mg/1 1; CHOLECALCIFEROL 20 ug/1 1; THIAMINE MONONITRATE 1.4 mg/1 1; PYRIDOXAL 5-PHOSPHATE 2.5 mg/1 1; FOLIC ACID 1000 ug/1 1; METHYLCOBALAMIN 1000 ug/1 1; CALCIUM CITRATE 200 mg/1 1; IRON 13 mg/1 1; POTASSIUM IODIDE 150 ug/1 1
INACTIVE INGREDIENTS: MICROCRYSTALLINE CELLULOSE; HYPROMELLOSE, UNSPECIFIED

Matervia

HEALTH CLAIM

Matervia Capsules - Prenatal/Postnatal

Dispensed By Prescription†

Serving Size: 2 Capsules

Servings per Container: 30

Other ingredients: Microcrystalline Cellulose (USP)

Vegetable Capsule (cellulose, purified water)

DESCRIPTION

Matervia is an orally administered prescription vitamin formulation for the clinical dietary management of suboptimal nutritional status
in patients where advanced folate supplementation is required and nutritional supplementation in physiologically stressful conditions for maintenance of good health is needed.

WARNING AND PRECAUTIONS

WARNING: Accidental overdose of iron-containing products is a leading cause of fatal poisoning in children under 6. KEEP THIS AND ALL DRUGS OUT OF THE REACH OF CHILDREN. In case of accidental overdose, call a doctor or poison control center immediately.

CONTRAINDICATIONS:

Matervia is contraindicated in patients with a known hypersensitivity to any of the ingredients. Do not take this product if you are presently taking mineral oil, unless directed by a doctor.

PRECAUTION:

Folic acid alone is improper therapy in the treatment of pernicious anemia and other megaloblastic anemias where vitamin B is deficient. Folic acid in doses above 1 mg daily may obscure pernicious anemia in that hematologic remission can occur while neurological manifestations progress. Matervia should only be used under the direction and supervision of a licensed medical practitioner.

ADVERSE REACTIONS

Allergic sensitization has been reported following both oral and parenteral administration of folic acid. You may report side effects by calling 1-800-519-8334 or the FDA by calling 1-800-FDA-1088.

DOSAGE & ADMINISTRATION

Suggested use is 2 capsules taken orally once daily or as prescribed by a licensed medical practitioner.

HOW SUPPLIED HEALTH CLAIM:

Matervia Capsules are available in 60-count bottles

NDC 72835-660-01

Dispensed by Prescription†
† This product is a prescription-folate with or without other dietary ingredients that – due to increased folate levels increased risk associated with masking of B12 deficiency (pernicious anemia) requires administration under the care of a licensed medical practitioner (61 FR 8760).

This product may be administered only under a physician’s supervision and all prescriptions using this product shall be pursuant to state statutes as applicable. The ingredients, indication or claims of this product are not to be construed to be drug claims.

STORAGE AND HANDLNG

Store Matervia at room temperature. Avoid excessive heat, light, and moisture.

Statements
These statements have not been evaluated by the Food and Drug Administration. This product is not intended to diagnose, treat, cure, or prevent any disease.

How Supplied
Matervia capsules are available in 60 count bottles. 72835-550-01

Manufactured for:
V2 Pharma, LLC
103 W Main Street
Hudson, MI 49247

PACKAGE LABEL

Matervia NDC 72835-660-01

The label for Matervia is shown below: